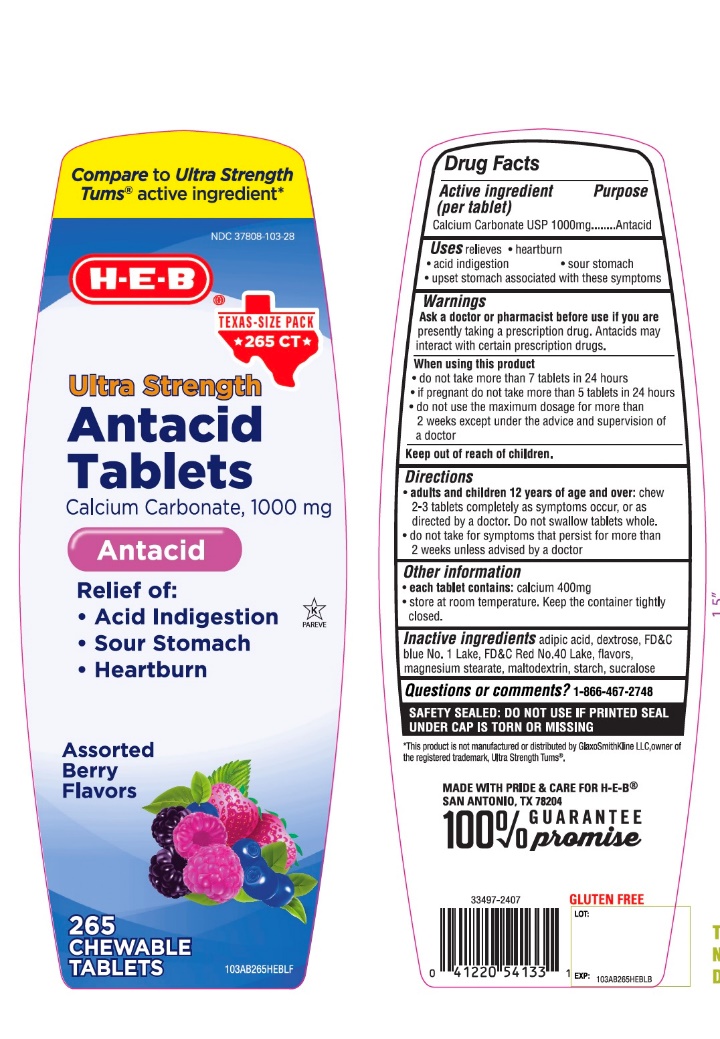 DRUG LABEL: HEB Antacid Calcium

NDC: 37808-103 | Form: TABLET, CHEWABLE
Manufacturer: HEB
Category: otc | Type: HUMAN OTC DRUG LABEL
Date: 20251003

ACTIVE INGREDIENTS: CALCIUM CARBONATE 1000 mg/1 1
INACTIVE INGREDIENTS: ADIPIC ACID; DEXTROSE, UNSPECIFIED FORM; FD&C BLUE NO. 1; FD&C RED NO. 40; MAGNESIUM STEARATE; MALTODEXTRIN; STARCH, CORN; SUCRALOSE

H-E-B Ultra Strength Antacid Calcium Carbonate Drug Facts

Active ingredient (per tablet)

Calcium Carbonate USP 1000mg

Purpose

Antacid

Uses

relieves

- heartburn
- acid indigestion
- sour stomach
- upset stomach associated with these symptoms

Ask a doctor or pharmacist before use if you are

presently taking a prescription drug. Antacids may interact with certain prescription drugs.

When using this product

- do not take more than 7 tablets in 24 hours
- if pregnant do not take more than 5 tablets in 24 hours
- do not use the maximum dosage for more than 2 weeks except under the advice and supervision of a doctor

Directions

- adults and children 12 years of age and over:chew 2-3 tablets, completely as symptoms occur, or as directed by a doctor. Do not swallow tablets whole.
- do not take for symptoms that persist for more than 2 weeks unless advised by a doctor

Other information

- each tablet contains: elemental calcium 400mg
- store at room temperature. Keep the container tightly closed.

Inactive ingredients

adipic acid, dextrose, FD&C blue no. 1, FD&C red no. 40, flavors, magnesium stearate, maltodextrin, starch, sucralose.

Questions or comments?

1-866-467-2748

Safety Sealed

Do not use if printed seal under cap is torn or missing

Package/Label Principal Display Panel

H-E-B®

NDC# 37808-103-28

Compare To Ultra Strength Tums®active ingredient*

ULTRA STRENGTH

Antacid Tablets

CALCIUM CARBONATE 1000 mg/Antacid

RELIEF OF:

- Acid Indigestion
- Sour Stomach
- Heartburn

Assorted Berry Flavors

GLUTEN FREE

265 CHEWABLE TABLETS

K PAREVE

100% GUARANTEE promise

MADE WITH PRIDE & CARE FOR H-E-B®SAN ANTONIA, TX 78204

*This product is not manufactured or distributed by GlaxoSmithKline LLC, owner of the registered trademark, Ultra Strength Tums®.